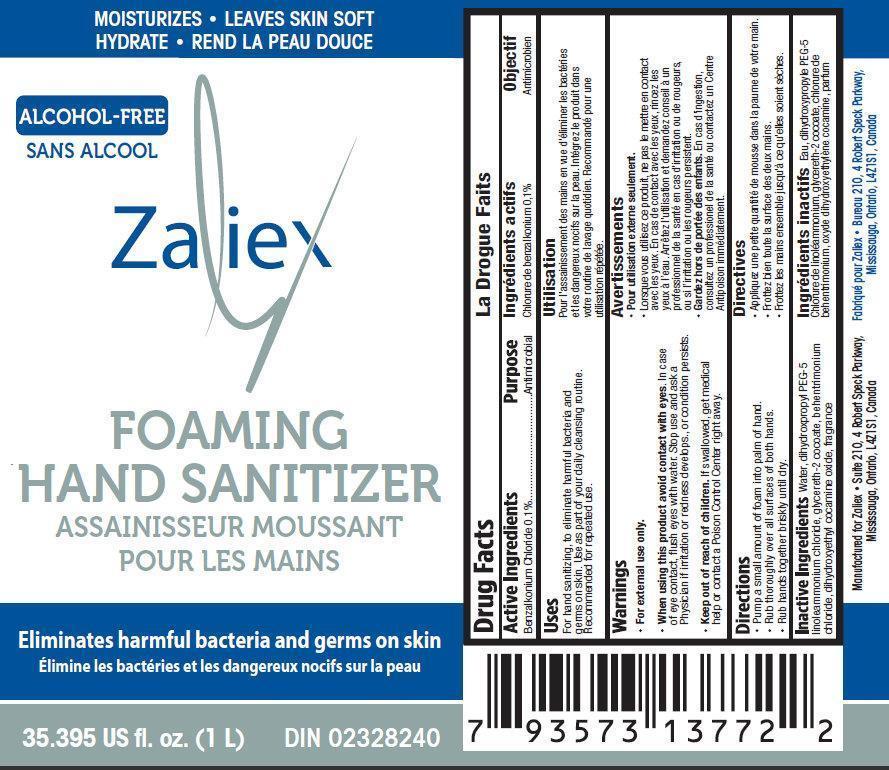 DRUG LABEL: Zaliex Alcohol-Free Foaming Hand Sanitizer
NDC: 76452-004 | Form: LIQUID
Manufacturer: SAS Healthcare Inc
Category: otc | Type: HUMAN OTC DRUG LABEL
Date: 20120912

ACTIVE INGREDIENTS: BENZALKONIUM CHLORIDE 0.1 mg/0.001 L
INACTIVE INGREDIENTS: WATER; DIHYDROXYPROPYL PEG-5 LINOLEAMMONIUM CHLORIDE; GLYCERETH-2 COCOATE; BEHENTRIMONIUM CHLORIDE; DIHYDROXYETHYL COCAMINE OXIDE

Zaliex Alcohol-Free Foaming Hand Sanitizer

Active Ingredient

Benzalkonium Chloride 0.1%

Purpose

Antimicrobial

Uses:

For hand sanitizing, to eliminate harmful bacteria and germs on skin.
Use as part of your daily cleansing routine.
Recommended for repeated use.

Warnings:

For external use only.

When using this product avoid contact with eyes. In case of eye contact, flush with water.

Stop use and ask a doctor if irritation or redness develops, or if condition persists.

Keep out of reach of children. If swallowed, get medical help or contact a Poison Control Center right away.

Directions:

- Pump a small amount of foam into palm of hand
- Run thoroughly over all surfaces of both hands
- Rub hands together briskly until dry

Inactive Ingredients:

Water, dihydroxypropyl PEG-5 linoleammonium chloride, glycereth-2 cocoate, behentrimonium chloride, dihydroxyethyl cocamine oxide, fragrance

Manufactured for:

Zaliex

Suite 210, 4 Robert Speck Parkway,

Mississauga, Ontario, L4Z1S1, Canada